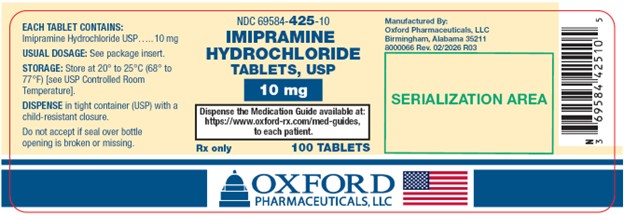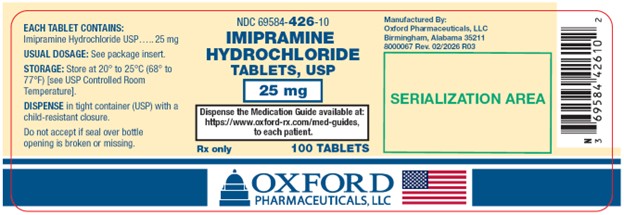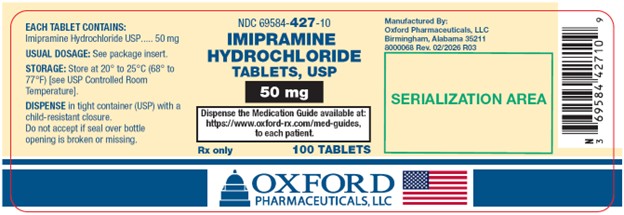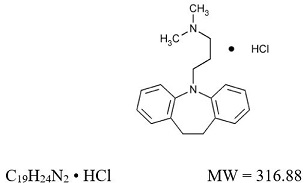 DRUG LABEL: Imipramine Hydrochloride
NDC: 69584-425 | Form: TABLET
Manufacturer: Oxford Pharmaceuticals, LLC
Category: prescription | Type: HUMAN PRESCRIPTION DRUG LABEL
Date: 20260217

ACTIVE INGREDIENTS: Imipramine Hydrochloride 10 mg/1 1
INACTIVE INGREDIENTS: Carnauba Wax; Silicon Dioxide; Lactose Monohydrate; Magnesium Stearate; Microcrystalline Cellulose 101; Sodium Starch Glycolate Type A Potato; Talc; Fd&C Yellow No. 6; Hypromellose, Unspecified; Lecithin, Soybean; Polyethylene Glycol, Unspecified; Polysorbate 80; Polyvinyl Alcohol, Unspecified; Titanium Dioxide; Ferric Oxide Yellow

IMIPRAMINE HYDROCHLORIDE TABLETS, USP
10 mg, 25 mg and 50 mg
Rx Only
Prescribing Information

BOXED WARNING

Suicidality and Antidepressant Drugs
Antidepressants increased the risk compared to placebo of suicidal thinking and behavior (suicidality) in children, adolescents, and young adults in short-term studies of major depressive disorder (MDD) and other psychiatric disorders. Anyone considering the use of imipramine hydrochloride or any other antidepressant in a child, adolescent, or young adult must balance this risk with the clinical need. Short-term studies did not show an increase in the risk of suicidality with antidepressants compared to placebo in adults beyond age 24; there was a reduction in risk with antidepressants compared to placebo in adults aged 65 and older. Depression and certain other psychiatric disorders are themselves associated with increases in the risk of suicide. Patients of all ages who are started on antidepressant therapy should be monitored appropriately and observed closely for clinical worsening, suicidality, or unusual changes in behavior. Families and caregivers should be advised of the need for close observation and communication with the prescriber. Imipramine hydrochloride is not approved for use in pediatric patients. (See WARNINGS: Clinical Worsening and Suicide Risk, PRECAUTIONS: Information for Patients, and PRECAUTIONS: Pediatric Use)

DESCRIPTION

Imipramine hydrochloride is supplied in tablet form for oral administration.

Imipramine hydrochloride USP, the original tricyclic antidepressant, is a member of the dibenzazepine group of compounds. It is designated 5-[3-(Dimethylamino)propyl]-10,11-dihydro-5H-dibenz [b,f]azepine monohydrochloride. Its structural formula is:

Imipramine hydrochloride USP is a white to off-white, odorless, or practically odorless crystalline powder. It is freely soluble in water and in alcohol, soluble in acetone, and insoluble in ether and in benzene.

Inactive Ingredients: Carnauba wax powder, colloidal silicon dioxide, FD & C yellow #6 Aluminum lake, hypromellose (10 mg), lactose monohydrate, lecithin (25 mg), magnesium stearate, microcrystalline cellulose, polyethylene glycol, polysorbate 80 (10 mg), polyvinyl alcohol (25 mg and 50 mg), sodium starch glycolate, talc, titanium dioxide, and yellow iron oxide (25 mg and 50 mg).

CLINICAL PHARMACOLOGY

The mechanism of action of imipramine hydrochloride is not definitely known. However, it does not act primarily by stimulation of the central nervous system. The clinical effect is hypothesized as being due to potentiation of adrenergic synapses by blocking uptake of norepinephrine at nerve endings. The mode of action of the drug in controlling childhood enuresis is thought to be apart from its antidepressant effect.

INDICATIONS AND USAGE

Depression-For the relief of symptoms of depression. Endogenous depression is more likely to be alleviated than other depressive states. One to three weeks of treatment may be needed before optimal therapeutic effects are evident.

Childhood Enuresis-May be useful as temporary adjunctive therapy in reducing enuresis in children aged 6 years and older, after possible organic causes have been excluded by appropriate tests. In patients having daytime symptoms of frequency and urgency, examination should include voiding cystourethrography and cystoscopy, as necessary. The effectiveness of treatment may decrease with continued drug administration.

CONTRAINDICATIONS

The concomitant use of monoamine oxidase inhibiting compounds is contraindicated. Hyperpyretic crises or severe convulsive seizures may occur in patients receiving such combinations. The potentiation of adverse effects can be serious, or even fatal. When it is desired to substitute imipramine hydrochloride in patients receiving a monoamine oxidase inhibitor, as long an interval should elapse as the clinical situation will allow, with a minimum of 14 days. Initial dosage should be low and increases should be gradual and cautiously prescribed.

The drug is contraindicated during the acute recovery period after a myocardial infarction. Patients with a known hypersensitivity to this compound should not be given the drug. The possibility of cross-sensitivity to other dibenzazepine compounds should be kept in mind.

WARNINGS

Clinical Worsening and Suicide Risk

Patients with major depressive disorder (MDD), both adult and pediatric, may experience worsening of their depression and/or the emergence of suicidal ideation and behavior (suicidality) or unusual changes in behavior, whether or not they are taking antidepressant medications, and this risk may persist until significant remission occurs. Suicide is a known risk of depression and certain other psychiatric disorders, and these disorders themselves are the strongest predictors of suicide. There has been a long-standing concern, however, that antidepressants may have a role in inducing worsening of depression and the emergence of suicidality in certain patients during the early phases of treatment. Pooled analyses of short-term placebo-controlled trials of antidepressant drugs. (SSRIs and others) showed that these drugs increase the risk of suicidal thinking and behavior (suicidality) in children, adolescents, and young adults (ages 18-24) with major depressive disorder (MDD) and other psychiatric disorders. Short-term studies did not show an increase in the risk of suicidality with antidepressants compared to placebo in adults beyond age 24; there was a reduction with antidepressants compared to placebo in adults aged 65 and older.

The pooled analyses of placebo-controlled trials in children and adolescents with MDD, obsessive compulsive disorder (OCD), or other psychiatric disorders included a total of 24 short-term trials of 9 antidepressant drugs in over 4400 patients. The pooled analyses of placebo-controlled trials in adults with MDD or other psychiatric disorders included a total of 295 short-term trials (median duration of 2 months) of 11 antidepressant drugs in over 77,000 patients. There was considerable variation in risk of suicidality among drugs, but a tendency toward an increase in the younger patients for almost all drugs studied. There were differences in absolute risk of suicidality across the different indications, with the highest incidence in MDD. The risk differences (drug vs. placebo), however, were relatively stable within age strata and across indications. These risk differences (drug-placebo difference in the number of cases of suicidality per 1000 patients treated) are provided in Table 1.

Table 1
Age Range | Drug-Placebo Difference in Number of Cases of Suicidality per 1000 Patients Treated
 | Increases Compared to Placebo
<18 | 14 additional cases
18-24 | 5 additional cases
 | Decreases Compared to Placebo
25-64 | 1 fewer case
≥65 | 6 fewer cases

No suicides occurred in any of the pediatric trials. There were suicides in the adult trials, but the number was not sufficient to reach any conclusion about drug effect on suicide.

It is unknown whether the suicidality risk extends to longer-term use, i.e., beyond several months. However, there is substantial evidence from placebo-controlled maintenance trials in adults with depression that the use of antidepressants can delay the recurrence of depression.

All patients being treated with antidepressants for any indication should be monitored appropriately and observed closely for clinical worsening, suicidality, and unusual changes in behavior, especially during the initial few months of a course of drug therapy, or at times of dose changes, either increases or decreases.

The following symptoms, anxiety, agitation, panic attacks, insomnia, irritability, hostility, aggressiveness, impulsivity, akathisia (psychomotor restlessness), hypomania, and mania, have been reported in adult and pediatric patients being treated with antidepressants for major depressive disorder as well as for other indications, both psychiatric and nonpsychiatric. Although a causal link between the emergence of such symptoms and either the worsening of depression and/or the emergence of suicidal impulses has not been established, there is concern that such symptoms may represent precursors to emerging suicidality.

Consideration should be given to changing the therapeutic regimen, including possibly discontinuing the medication, in patients whose depression is persistently worse, or who are experiencing emergent suicidality or symptoms that might be precursors to worsening depression or suicidality, especially if these symptoms are severe, abrupt in onset, or were not part of the patient's presenting symptoms.

Families and caregivers of patients being treated with antidepressants for major depressive disorder or other indications, both psychiatric and nonpsychiatric, should be alerted about the need to monitor patients for the emergence of agitation, irritability, unusual changes in behavior, and the other symptoms described above, as well as the emergence of suicidality, and to report such symptoms immediately to health care providers. Such monitoring should include daily observation by families and caregivers. Prescriptions for imipramine hydrochloride should be written for the smallest quantity of tablets consistent with good patient management, in order to reduce the risk of overdose.

Screening Patients for Bipolar Disorder-A major depressive episode may be the initial presentation of bipolar disorder. It is generally believed (though not established in controlled trials) that treating such an episode with an antidepressant alone may increase the likelihood of precipitation of a mixed/manic episode in patients at risk for bipolar disorder. Whether any of the symptoms described above represent such a conversion is unknown. However, prior to initiating treatment with an antidepressant, patients with depressive symptoms should be adequately screened to determine if they are at risk for bipolar disorder; such screening should include a detailed psychiatric history, including a family history of suicide, bipolar disorder, and depression. It should be noted that imipramine hydrochloride is not approved for use in treating bipolar depression.

Hyponatremia – Hyponatremia has occurred as a result of treatment with imipramine hydrochloride tablets. In many cases, hyponatremia appears to be the result of the syndrome of inappropriate antidiuretic hormone secretion (SIADH). Signs and symptoms of hyponatremia include headache, difficulty concentrating, memory impairment, confusion, weakness, and unsteadiness, which may lead to falls. Signs and symptoms associated with more severe and/or acute cases have included syncope, seizure, coma, respiratory arrest, and death.

In patients with symptomatic hyponatremia, discontinue imipramine hydrochloride tablets and institute appropriate medical intervention. Elderly patients, patients taking diuretics, and those who are volume-depleted may be at greater risk of developing hyponatremia with imipramine hydrochloride tablets.

Angle-Closure Glaucoma – The pupillary dilation that occurs following use of many antidepressant drugs including Imipramine hydrochloride may trigger an angle-closure attack in a patient with anatomically narrow angles who does not have a patent iridectomy.

Children-A dose of 2.5 mg/kg/day of imipramine hydrochloride should not be exceeded in childhood. ECG changes of unknown significance have been reported in pediatric patients with doses twice this amount.

Extreme caution should be used when this drug is given to: patients with cardiovascular disease because of the possibility of conduction defects, arrhythmias, congestive heart failure, myocardial infarction, strokes, and tachycardia. These patients require cardiac surveillance at all dosage levels of the drug;

Patients with history of urinary retention, or history of narrow-angle glaucoma because of the drug's anticholinergic properties; hyperthyroid patients or those on thyroid medication because of the possibility of cardiovascular toxicity;

patients with a history of seizure disorder because this drug has been shown to lower the seizure threshold;

patients receiving guanethidine, clonidine, or similar agents, since imipramine hydrochloride may block the pharmacologic effects of these drugs;

patients receiving methylphenidate hydrochloride. Since methylphenidate hydrochloride may inhibit the metabolism of imipramine hydrochloride, downward dosage adjustment of imipramine hydrochloride may be required when given concomitantly with methylphenidate hydrochloride.

Imipramine hydrochloride may enhance the CNS depressant effects of alcohol. Therefore, it should be borne in mind that the dangers inherent in a suicide attempt or accidental overdosage with the drug may be increased for the patient who uses excessive amounts of alcohol. (See PRECAUTIONS.)

Since imipramine hydrochloride may impair the mental and/or physical abilities required for the performance of potentially hazardous tasks, such as operating an automobile or machinery, the patient should be cautioned accordingly.

PRECAUTIONS

General

An ECG recording should be taken prior to the initiation of larger-than-usual doses of imipramine hydrochloride and at appropriate intervals thereafter until steady state is achieved. (Patients with any evidence of cardiovascular disease require cardiac surveillance at all dosage levels of the drug. See WARNINGS.) Elderly patients and patients with cardiac disease or a prior history of cardiac disease are at special risk of developing the cardiac abnormalities associated with the use of imipramine hydrochloride.

It should be kept in mind that the possibility of suicide in seriously depressed patients is inherent in the illness and may persist until significant remission occurs. Such patients should be carefully supervised during the early phase of treatment with imipramine hydrochloride, and may require hospitalization. Prescriptions should be written for the smallest amount feasible. Hypomanic or manic episodes may occur, particularly in patients with cyclic disorders. Such reactions may necessitate discontinuation of the drug. If needed, imipramine hydrochloride may be resumed in lower dosage when these episodes are relieved.

Administration of a tranquilizer may be useful in controlling such episodes.

An activation of the psychosis may occasionally be observed in schizophrenic patients and may require reduction of dosage and the addition of a phenothiazine.

Concurrent administration of imipramine hydrochloride with electroshock therapy may increase the hazards; such treatment should be limited to those patients for whom it is essential, since there is limited clinical experience.

Patients taking imipramine hydrochloride should avoid excessive exposure to sunlight since there have been reports of photosensitization.

Both elevation and lowering of blood sugar levels have been reported with imipramine hydrochloride use.

Imipramine hydrochloride should be used with caution in patients with significantly impaired renal or hepatic function.

Patients who develop a fever and a sore throat during therapy with imipramine hydrochloride should have leukocyte and differential blood counts performed. Imipramine hydrochloride should be discontinued if there is evidence of pathological neutrophil depression.

Prior to elective surgery, imipramine hydrochloride should be discontinued for as long as the clinical situation will allow.

Information for Patients

Prescribers or other health professionals should inform patients, their families, and their caregivers about the benefits and risks associated with treatment with imipramine hydrochloride and should counsel them in its appropriate use. A patient Medication Guide about “Antidepressant Medicines, Depression and other Serious Mental Illnesses, and Suicidal Thoughts or Actions” is available for imipramine hydrochloride. The prescriber or health professional should instruct patients, their families, and their caregivers to read the Medication Guide and should assist them in understanding its contents. Patients should be given the opportunity to discuss the contents of the Medication Guide and to obtain answers to any questions they may have. The complete text of the Medication Guide is reprinted at the end of this document.

Patients should be advised of the following issues and asked to alert their prescriber if these occur while taking imipramine hydrochloride.

Patients should be advised that taking imipramine hydrochloride can cause mild pupillary dilation, which in susceptible individuals, can lead to an episode of angle-closure glaucoma. Pre-existing glaucoma is almost always open-angle glaucoma because angle-closure glaucoma, when diagnosed, can be treated definitively with iridectomy. Open-angle glaucoma is not a risk factor for angle-closure glaucoma. Patients may wish to be examined to determine whether they are susceptible to angle closure, and have a prophylactic procedure (e.g., iridectomy), if they are susceptible.

Clinical Worsening and Suicide Risk-Patients, their families, and their caregivers should be encouraged to be alert to the emergence of anxiety, agitation, panic attacks, insomnia, irritability, hostility, aggressiveness, impulsivity, akathisia (psychomotor restlessness), hypomania, mania, other unusual changes in behavior, worsening of depression, and suicidal ideation, especially early during antidepressant treatment and when the dose is adjusted up or down. Families and caregivers of patients should be advised to look for the emergence of such symptoms on a day-to-day basis, since changes may be abrupt. Such symptoms should be reported to the patient's prescriber or health professional, especially if they are severe, abrupt in onset, or were not part of the patient's presenting symptoms. Symptoms such as these may be associated with an increased risk for suicidal thinking and behavior and indicate a need for very close monitoring and possibly changes in the medication.

Drug Interactions

Drugs Metabolized by P450 2D6: The biochemical activity of the drug metabolizing isozyme cytochrome P450 2D6 (debrisoquin hydroxylase) is reduced in a subset of the Caucasian population (about 7% to 10% of Caucasians are so-called "poor metabolizers"); reliable estimates of the prevalence of reduced P450 2D6 isozyme activity among Asian, African, and other populations are not yet available. Poor metabolizers have higher than expected plasma concentrations of tricyclic antidepressants (TCAs) when given usual doses. Depending on the fraction of drug metabolized by P450 2D6, the increase in plasma concentration may be small, or quite large (8-fold increase in plasma AUC of the TCA).

In addition, certain drugs inhibit the activity of this isozyme and make normal metabolizers resemble poor metabolizers. An individual who is stable on a given dose of TCA may become abruptly toxic when given one of these inhibiting drugs as concomitant therapy. The drugs that inhibit cytochrome P450 2D6 include some that are not metabolized by the enzyme (quinidine; cimetidine) and many that are substrates for P450 2D6 (many other antidepressants, phenothiazines, and the Type 1C antiarrhythmics propafenone and flecainide). While all the selective serotonin reuptake inhibitors (SSRIs), e.g., fluoxetine, sertraline, and paroxetine, inhibit P450 2D6, they may vary in the extent of inhibition. The extent to which SSRI-TCA interaction may pose clinical problems will depend on the degree of inhibition and the pharmacokinetics of the SSRI involved. Nevertheless, caution is indicated in the coadministration of TCAs with any of the SSRIs and also in switching from one class to the other. Of particular importance, sufficient time must elapse before initiating TCA treatment in a patient being withdrawn from fluoxetine, given the long half-life of the parent and active metabolite (at least 5 weeks may be necessary).

Concomitant use of tricyclic antidepressants with drugs that can inhibit cytochrome P450 2D6 may require lower doses than usually prescribed for either the tricyclic antidepressant or the other drug. Furthermore, whenever one of these other drugs is withdrawn from co-therapy, an increased dose of tricyclic antidepressant may be required. It is desirable to monitor TCA plasma levels whenever a TCA is going to be co-administered with another drug known to be an inhibitor of P450 2D6.

The plasma concentration of imipramine may increase when the drug is given concomitantly with hepatic enzyme inhibitors (e.g., cimetidine, fluoxetine) and decrease by concomitant administration with hepatic enzyme inducers (e.g., barbiturates, phenytoin), and adjustment of the dosage of imipramine may therefore be necessary.

In occasional susceptible patients or in those receiving anticholinergic drugs (including antiparkinsonism agents) in addition, the atropine-like effects may become more pronounced (e.g., paralytic ileus). Close supervision and careful adjustment of dosage is required when imipramine hydrochloride is administered concomitantly with anticholinergic drugs.

Avoid the use of preparations, such as decongestants and local anesthetics, that contain any sympathomimetic amine (e.g., epinephrine, norepinephrine), since it has been reported that tricyclic antidepressants can potentiate the effects of catecholamines.

Caution should be exercised when imipramine hydrochloride is used with agents that lower blood pressure. Imipramine hydrochloride may potentiate the effects of CNS depressant drugs.

Patients should be warned that imipramine hydrochloride may enhance the CNS depressant effects of alcohol. (see WARNINGS.)

Pregnancy

Animal reproduction studies have yielded inconclusive results (see also ANIMAL PHARMACOLOGY & TOXICOLOGY.)

There have been no well-controlled studies conducted with pregnant women to determine the effect of imipramine hydrochloride on the fetus. However, there have been clinical reports of congenital malformations associated with the use of the drug. Although a causal relationship between these effects and the drug could not be established, the possibility of fetal risk from the maternal ingestion of imipramine hydrochloride cannot be excluded. Therefore, imipramine hydrochloride should be used in women who are or might become pregnant only if the clinical condition clearly justifies potential risk to the fetus.

Nursing Mothers

Limited data suggest that imipramine hydrochloride is likely to be excreted in human breast milk. As a general rule, a woman taking a drug should not nurse since the possibility exists that the drug may be excreted in breast milk and be harmful to the child.

Pediatric Use

Safety and effectiveness in the pediatric population other than pediatric patients with nocturnal enuresis have not been established (see BOX WARNING and WARNINGS: Clinical Worsening and Suicide Risk). Anyone considering the use of imipramine hydrochloride in a child or adolescent must balance the potential risks with the clinical need.

The safety and effectiveness of the drug as temporary adjunctive therapy for nocturnal enuresis in pediatric patients less than 6 years of age has not been established.

The safety of the drug for long-term, chronic use as adjunctive therapy for nocturnal enuresis in pediatric patients 6 years of age or older has not been established; consideration should be given to instituting a drug-free period following an adequate therapeutic trial with a favorable response.

A dose of 2.5 mg/kg/day should not be exceeded in childhood. ECG changes of unknown significance have been reported in pediatric patients with doses twice this amount.

Geriatric Use

In the literature, there were four well-controlled, randomized, double-blind, parallel group comparison clinical studies done with imipramine hydrochloride in the elderly population. There was a total number of 651 subjects included in these studies. These studies did not provide a comparison to younger subjects. There were no additional adverse experiences identified in the elderly.

Clinical studies of imipramine hydrochloride in the original application did not include sufficient numbers of subjects aged 65 and over to determine whether they respond differently from younger subjects. Post-marketing clinical experience has not identified differences in responses between the elderly and younger subjects. In general, dose selection for the elderly should be cautious, usually starting at the low end of the dosing range, reflecting greater frequency of decreased hepatic, renal, or cardiac function, and of concomitant disease or other drug therapy.

(See also DOSAGE AND ADMINISTRATION: Adolescent and Geriatric Patients)

(See also PRECAUTIONS: General)

ADVERSE REACTIONS

Note-Although the listing which follows includes a few adverse reactions which have not been reported with this specific drug, the pharmacological similarities among the tricyclic antidepressant drugs require that each of the reactions be considered when imipramine hydrochloride is administered.

Cardiovascular: Orthostatic hypotension, hypertension, tachycardia, palpitation, myocardial infarction, arrhythmias, heart block, ECG changes, precipitation of congestive heart failure, stroke.

Psychiatric: Confusional states (especially in the elderly) with hallucinations, disorientation, delusions; anxiety, restlessness, agitation; insomnia and nightmares; hypomania; exacerbation of psychosis.

Neurological: Numbness, tingling, paresthesias of extremities; incoordination, ataxia, tremors; peripheral neuropathy; extrapyramidal symptoms; seizures, alterations in EEG patterns; tinnitus.

Anticholinergic: Dry mouth, and, rarely, associated sublingual adenitis; blurred vision, disturbances of accommodation, mydriasis; constipation, paralytic ileus; urinary retention, delayed micturition, dilation of the urinary tract.

Allergic: Skin rash, petechiae, urticaria, itching, photosensitization; edema (general or of face and tongue); drug fever; cross-sensitivity with desipramine.

Hematologic: Bone marrow depression including agranulocytosis; eosinophilia; purpura; thrombocytopenia.

Gastrointestinal: Nausea and vomiting, anorexia, epigastric distress, diarrhea; peculiar taste, stomatitis, abdominal cramps, black tongue.

Endocrine: Gynecomastia in the male; breast enlargement and galactorrhea in the female; increased or decreased libido, impotence; testicular swelling; elevation or depression of blood sugar levels; inappropriate antidiuretic hormone (ADH) secretion syndrome.

Other: Jaundice (simulating obstructive); altered liver function; weight gain or loss; perspiration; flushing; urinary frequency; drowsiness, dizziness, weakness and fatigue; headache; parotid swelling; alopecia; proneness to falling, hyponatremia.

Withdrawal Symptoms: Though not indicative of addiction, abrupt cessation of treatment after prolonged therapy may produce nausea, headache, and malaise.

Note-In enuretic children treated with imipramine hydrochloride the most common adverse reactions have been nervousness, sleep disorders, tiredness, and mild gastrointestinal disturbances. These usually disappear during continued drug administration or when dosage is decreased. Other reactions which have been reported include constipation, convulsions, anxiety, emotional instability, syncope, and collapse. All of the adverse effects reported with adult use should be considered.

Postmarketing Experience

The following adverse drug reaction has been reported during post-approval use of imipramine hydrochloride. Because this reaction is reported voluntarily from a population of uncertain size, it is not always possible to reliably estimate frequency.

Eye disorders: angle-closure glaucoma

OVERDOSAGE

Deaths may occur from overdosage with this class of drugs. Multiple drug ingestion (including alcohol) is common in deliberate tricyclic overdose. As the management is complex and changing, it is recommended that the physician contact a poison control center for current information on treatment. Signs and symptoms of toxicity develop rapidly after tricyclic overdose. Therefore, hospital monitoring is required as soon as possible.

Children have been reported to be more sensitive than adults to an acute overdosage of imipramine hydrochloride. An acute overdose of any amount in infants or young children, especially, must be considered serious and potentially fatal.

Manifestations
These may vary in severity depending upon factors such as the amount of drug absorbed, the age of the patient, and the interval between drug ingestion and the start of treatment. Critical manifestations of overdose include cardiac dysrhythmias, severe hypotension, convulsions, and CNS depression including coma. Changes in the electrocardiogram, particularly in QRS axis or width, are clinically significant indicators of tricyclic toxicity.

Other CNS manifestations may include drowsiness, stupor, ataxia, restlessness, agitation, hyperactive reflexes, muscle rigidity, athetoid and choreiform movements.

Cardiac abnormalities may include tachycardia and signs of congestive failure. Respiratory depression, cyanosis, shock, vomiting, hyperpyrexia, mydriasis, and diaphoresis may also be present.

Management
Obtain an ECG and immediately initiate cardiac monitoring. Protect the patient’s airway, establish an intravenous line and initiate gastric decontamination. A minimum of 6 hours of observation with cardiac monitoring and observation for signs of CNS or respiratory depression, hypotension, cardiac dysrhythmias and/or conduction blocks, and seizures is necessary. If signs of toxicity occur at anytime during this period, extended monitoring is required. There are case reports of patients succumbing to fatal dysrhythmias late after overdose; these patients had clinical evidence of significant poisoning prior to death and most received inadequate gastrointestinal decontamination. Monitoring of plasma drug levels should not guide management of the patient.

Gastrointestinal Decontamination-All patients suspected of tricyclic overdose should receive gastrointestinal decontamination. This should include large volume gastric lavage followed by activated charcoal. If consciousness is impaired, the airway should be secured prior to lavage. Emesis is contraindicated.

Cardiovascular-A maximal limb-lead QRS duration of ≥ 0.10 seconds may be the best indication of the severity of the overdose. Intravenous sodium bicarbonate should be used to maintain the serum pH in the range of 7.45 to 7.55. If the pH response is inadequate, hyperventilation may also be used. Concomitant use of hyperventilation and sodium bicarbonate should be done with extreme caution, with frequent pH monitoring. A pH >7.60 or a pCO2 < 20 mmHg is undesirable. Dysrhythmias unresponsive to sodium bicarbonate therapy/hyperventilation may respond to lidocaine, bretylium, or phenytoin. Type 1A and 1C antiarrhythmics are generally contraindicated (e.g., quinidine, disopyramide, and procainamide).

In rare instances, hemoperfusion may be beneficial in acute refractory cardiovascular instability in patients with acute toxicity. However, hemodialysis, peritoneal dialysis, exchange transfusions, and forced diuresis generally have been reported as ineffective in tricyclic poisoning.

CNS-In patients with CNS depression, early intubation is advised because of the potential for abrupt deterioration. Seizures should be controlled with benzodiazepines, or if these are ineffective, other anticonvulsants (e.g., phenobarbital, phenytoin). Physostigmine is not recommended except to treat life-threatening symptoms that have been unresponsive to other therapies, and then only in consultation with a poison control center.

Psychiatric Follow-up-Since overdosage is often deliberate, patients may attempt suicide by other means during the recovery phase. Psychiatric referral may be appropriate.

Pediatric Management-The principles of management of child and adult overdosages are similar. It is strongly recommended that the physician contact the local poison control center for specific pediatric treatment.

DOSAGE AND ADMINISTRATION

Depression
Lower dosages are recommended for elderly patients and adolescents. Lower dosages are also recommended for outpatients as compared to hospitalized patients who will be under close supervision. Dosage should be initiated at a low level and increased gradually, noting carefully the clinical response and any evidence of intolerance. Following remission, maintenance medication may be required for a longer period of time, at the lowest dose that will maintain remission.

Usual Adult Dose:
Hospitalized patients-Initially, 100 mg/day in divided doses gradually increased to 200 mg/day as required. If no response after two weeks, increase to 250 to 300 mg/day.

Outpatients-Initially, 75 mg/day increased to 150 mg/day. Dosages over 200 mg/day are not recommended. Maintenance, 50 to 150 mg/day.

Adolescent and Geriatric Patients-Initially, 30 to 40 mg/day; it is generally not necessary to exceed 100 mg/day.

Childhood Enuresis
Initially, an oral dose of 25 mg/day should be tried in children aged 6 and older. Medication should be given one hour before bedtime. If a satisfactory response does not occur within one week, increase the dose to 50 mg nightly in children under 12 years; children over 12 may receive up to 75 mg nightly. A daily dose greater than 75 mg does not enhance efficacy and tends to increase side effects. Evidence suggests that in early night bedwetters, the drug is more effective given earlier and in divided amounts, i.e., 25 mg in midafternoon, repeated at bedtime. Consideration should be given to instituting a drug free period following an adequate therapeutic trial with a favorable response. Dosage should be tapered off gradually rather than abruptly discontinued; this may reduce the tendency to relapse. Children who relapse when the drug is discontinued do not always respond to a subsequent course of treatment.

A dose of 2.5 mg/kg/day should not be exceeded. ECG changes of unknown significance have been reported in pediatric patients with doses twice this amount.

The safety and effectiveness of imipramine hydrochloride as temporary adjunctive therapy for nocturnal enuresis in children less than 6 years of age has not been established.

HOW SUPPLIED

Imipramine Hydrochloride Tablets, USP

10 mg – Peach, round, film coated, biconvex tablets debossed “425” on one side and “O” on the other. Available in:
Bottles of 100 ………..…… … NDC-69584-425-10
Bottles of 1000 ………..……… NDC-69584-425-90

25 mg – Light orange, round, film coated, biconvex tablets debossed “426” on one side and “O” on the other. Available in:
Bottles of 100 ……..……… … NDC-69584-426-10
Bottles of 1000 ………..……… NDC-69584-426-90

50 mg – Orange, round, film coated, biconvex tablets debossed “427” on one side and “O” on the other. Available in:
Bottles of 100 …………..… … NDC-69584-427-10
Bottles of 1000 ………..……… NDC-69584-427-90

Store at 20°C to 25°C (68° to 77°F) [See USP Controlled Room Temperature].

Dispense in a tight container (USP) with a child-resistant closure.

ANIMAL PHARMACOLOGY & TOXICOLOGY

A. Acute: Oral LD50 ranges are as follows:

Rat 355 to 682 mg/kg
Dog 100 to 215 mg/kg

Depending on the dosage in both species, toxic signs proceeded progressively from depression, irregular respiration and ataxia to convulsions and death.

B. Reproduction/Teratogenic: The overall evaluation may be summed up in the following manner:

Oral: Independent studies in three species (rat, mouse, and rabbit) revealed that when imipramine hydrochloride is administered orally in doses up to approximately 2-1/2 times the maximum human dose in the first 2 species and up to 25 times the maximum human dose in the third species, the drug is essentially free from teratogenic potential. In the three species studied, only one instance of fetal abnormality occurred (in the rabbit) and in that study there was likewise an abnormality in the control group. However, evidence does exist from the rat studies that some systemic and embryotoxic potential is demonstrable. This is manifested by reduced litter size, a slight increase in the stillborn rate, and a reduction in the mean birth weight.

Manufactured by:
Oxford Pharmaceuticals LLC
Birmingham, AL 35211 USA
8200007
06/25
Rev 04

Medication Guide

Antidepressant Medicines, Depression and other Serious Mental Illnesses,
and Suicidal Thoughts or Actions

Dispense with Medication Guide available at: https://www.oxford-rx.com/med-guides

Read the Medication Guide that comes with your or your family member’s antidepressant medicine. This Medication Guide is only about the risk of suicidal thoughts and actions with antidepressant medicines. Talk to your family member’s, or your healthcare provider about:

- all risks and benefits of treatment with antidepressant medicines
- all treatment choices for depression or other serious mental illness

What is the most important information I should know about antidepressant medicines, depression and other serious mental illnesses, and suicidal thoughts or actions?

1. | Antidepressant medicines may increase suicidal thoughts or actions in some children, teenagers, and young adults within the first few months of treatment.
2. | Depression and other serious mental illnesses are the most important causes of suicidal thoughts and actions. Some people may have a particularly high risk of having suicidal thoughts or actions. These include people who have (or have a family history of) bipolar illness (also called manic-depressive illness) or suicidal thoughts or actions.
3. | How can I watch for and try to prevent suicidal thoughts and actions in myself or a family member?
• | Pay close attention to any changes, especially sudden changes, in mood, behaviors, thoughts, or feelings. This is very important when an antidepressant medicine is started or when the dose is changed.
• | Call the healthcare provider right away to report new or sudden changes in mood, behavior, thoughts, or feelings.
• | Keep all follow-up visits with the healthcare provider as scheduled. Call the healthcare provider between visits as needed, especially if you have concerns about symptoms.

Call a healthcare provider right away if you or your family member has any of the following symptoms, especially if they are new, worse, or worry you:

- thoughts about suicide or dying
- attempts to commit suicide
- new or worse depression
- new or worse anxiety
- feeling very agitated or restless
- panic attacks
- trouble sleeping (insomnia)
- new or worse irritability
- acting aggressive, being angry, or violent
- acting on dangerous impulses

- an extreme increase in activity and talking (mania)
- other unusual changes in behavior or mood
- Low salt (sodium) levels in the blood. Elderly people may be at greater risk for this. Symptoms may include:
  - headache
  - weakness or feeling unsteady
  - confusion, problems concentrating or thinking or memory problems
- Visual problems: eye pain, changes in vision, swelling or redness in or around the eye

Who should not take imipramine hydrochloride?

Do not take imipramine hydrochloride if you:

- take a monoamine oxidase inhibitor (MAOI). Ask your healthcare provider or
  pharmacist if you are not sure if you take an MAOI, including the antibiotic linezolid.
  - Do not take an MAOI within 2 weeks of stopping imipramine
    hydrochloride unless directed to do so by your physician.
  - Do not start imipramine hydrochloride if you stopped taking an MAOI
    in the last 2 weeks unless directed to do so by your physician.

What else do I need to know about antidepressant medicines?

- Never stop an antidepressant medicine without first talking to a healthcare provider. Stopping an antidepressant medicine suddenly can cause other symptoms.
- Visual problems: Only some people are at risk for these problems. You may want to undergo an eye examination to see if you are at risk and receive preventative treatment if you are.
- Antidepressants are medicines used to treat depression and other illnesses. It is important to discuss all the risks of treating depression and also the risks of not treating it. Patients and their families or other caregivers should discuss all treatment choices with the healthcare provider, not just the use of antidepressants.
- Antidepressant medicines have other side effects. Talk to the healthcare provider about the side effects of the medicine prescribed for you or your family member.
- Antidepressant medicines can interact with other medicines. Know all of the medicines that you or your family member takes. Keep a list of all medicines to show the healthcare provider. Do not start new medicines without first checking with your healthcare provider.
- Not all antidepressant medicines prescribed for children are FDA approved for use in children. Talk to your child’s healthcare provider for more information.
- Tell your healthcare provider if you have low sodium levels in your blood during treatment with imipramine hydrochloride tablets.

Call your doctor for medical advice about side effects. You may report side effects to FDA at 1-800- FDA-1088.

This Medication Guide has been approved by the U.S. Food and Drug Administration for all antidepressants.

Manufactured by:
Oxford Pharmaceuticals LLC
Birmingham, AL 35211 USA
8200019
06/25
Rev 03

PRINCIPAL DISPLAY PANEL 10 MG TABLETS 100’S

NDC-69584-425-10
IMIPRAMINE
HYDROCHLORIDE
TABLETS USP
10 mg
Dispense the Medication Guide available at:
https://www.oxford-rx.com/med-guides,
to each patient.
Rx only 100 TABLETS
OXFORD
PHARMACEUTICALS, LLC
EACH TABLET CONTAINS:
Imipramine Hydrochloride USP... 10 mg
USUAL DOSAGE: See package insert.
STORAGE: Store at 20°C to 25°C (68° to 77°F)
[See USP Controlled Room Temperature].
DISPENSE in tight container (USP) with a
child-resistant closure.
Do not accept if seal over bottle
opening is broken or missing.
Manufactured by:
Oxford Pharmaceuticals, LLC
Birmingham, Alabama 35211
8000066 Rev. 02/2026 R03

PRINCIPAL DISPLAY PANEL 25 MG TABLETS 100’S

NDC-69584-426-10
IMIPRAMINE
HYDROCHLORIDE
TABLETS USP
25 mg
Dispense the Medication Guide available at:
https://www.oxford-rx.com/med-guides,
to each patient.
Rx only 100 TABLETS
OXFORD
PHARMACEUTICALS, LLC
EACH TABLET CONTAINS:
Imipramine Hydrochloride USP... 25 mg
USUAL DOSAGE: See package insert.
STORAGE: Store at 20°C to 25°C (68° to 77°F)
[See USP Controlled Room Temperature].
DISPENSE in tight container (USP) with a
child-resistant closure.
Do not accept if seal over bottle
opening is broken or missing.
Manufactured by:
Oxford Pharmaceuticals, LLC
Birmingham, Alabama 35211
8000067 Rev. 02/2026 R03

PRINCIPAL DISPLAY PANEL 50 MG TABLETS 100’S

NDC-69584-427-10
IMIPRAMINE
HYDROCHLORIDE
TABLETS USP
50 mg
Dispense the Medication Guide available at:
https://www.oxford-rx.com/med-guides,
to each patient.
Rx only 100 TABLETS
OXFORD PHARMACEUTICALS, LLC
EACH TABLET CONTAINS:
Imipramine Hydrochloride USP... 50 mg
USUAL DOSAGE: See package insert.
STORAGE: Store at 20°C to 25°C (68° to 77°F)
[See USP Controlled Room Temperature].
DISPENSE in tight container (USP) with a
child-resistant closure.
Do not accept if seal over bottle
opening is broken or missing.
Manufactured by:
Oxford Pharmaceuticals, LLC
Birmingham, Alabama 35211
8000068 Rev. 02/2026 R03